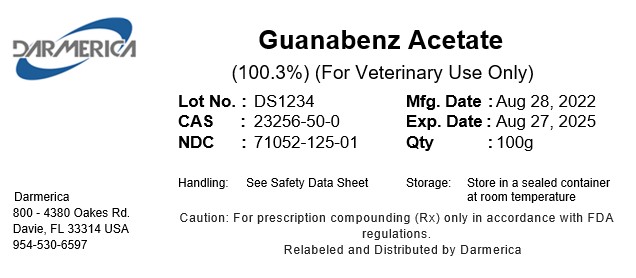 DRUG LABEL: Guanabenz Acetate
NDC: 71052-125 | Form: POWDER
Manufacturer: DARMERICA, LLC
Category: other | Type: BULK INGREDIENT - ANIMAL DRUG
Date: 20251121

ACTIVE INGREDIENTS: GUANABENZ ACETATE 1 kg/1 kg

Guanabenz Acetate